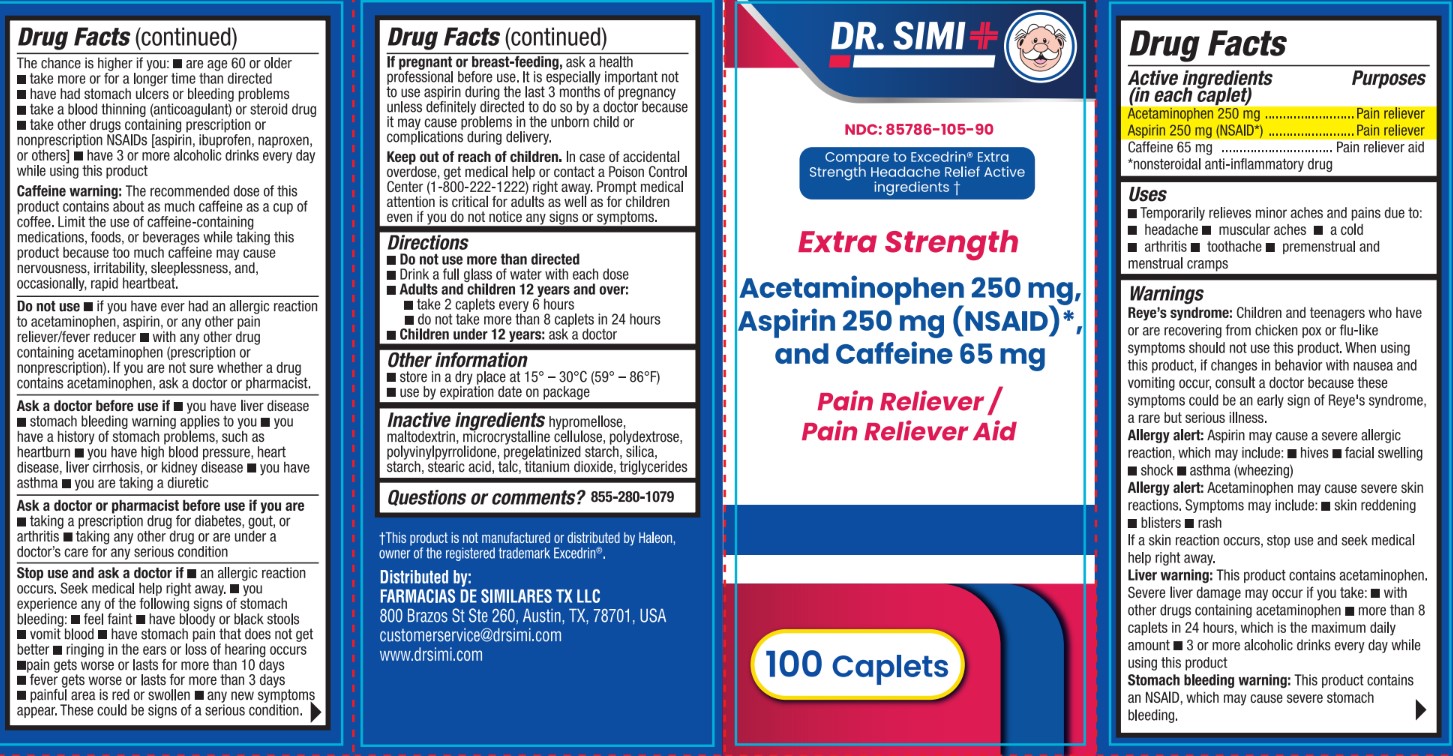 DRUG LABEL: Dr Simi Extra Strength Acetaminophen 250 mg, Aspirin 250 mg, and Caffeine 65 mg
NDC: 85786-105 | Form: TABLET, COATED
Manufacturer: Farmacias De Similares TX LLC
Category: otc | Type: HUMAN OTC DRUG LABEL
Date: 20260121

ACTIVE INGREDIENTS: ACETAMINOPHEN 250 mg/1 1; ASPIRIN 250 mg/1 1; CAFFEINE 65 mg/1 1
INACTIVE INGREDIENTS: MEDIUM-CHAIN TRIGLYCERIDES; MICROCRYSTALLINE CELLULOSE; STARCH, CORN; SILICON DIOXIDE; STEARIC ACID; MALTODEXTRIN; POVIDONE K30; POLYDEXTROSE; TITANIUM DIOXIDE; TALC; HYPROMELLOSES

Active Ingredients (in each caplet)

Acetaminophen 250 mg
Aspirin 250 mg (NSAID*)
Caffeine 65 mg
*nonsteroidal anti-inflammatory drug

Purposes

Acetaminophen 250 mg...............................Pain reliever
Aspirin 250 mg (NSAID*).............................Pain reliever
Caffeine 65 mg............................................Pain reliever aid
*nonsteroidal anti-inflammatory drug

Uses

Temporarily relieves minor aches and pains due to:
- headache

- muscular aches

- a cold
- arthritis

- toothache

- premenstrual and menstrual cramps

Warnings

Reye's syndrome: Children and teenagers who have or are recovering from chicken pox or flu-like symptoms should not use this product. When using this product, if changes in behavior with nausea and vomiting occur, consult a doctor because these symptoms could be an early sign of Reye's syndrome, a rare but serious illness.

Allergy alert: Aspirin may cause a severe allergic reaction, which may include: - hives - facial swelling - shock - asthma (wheezing)

Allergy alert: Acetaminophen may cause severe skinreactions. Symptoms may include: - skin reddening - blisters - rash
If a skin reaction occurs, stop use and seek medical help right away.

Liver warning: This product contains acetaminophen. Severe liver damage may occur if you take: - with other drugs containing acetaminophen - more than 8 caplets in 24 hours, which is the maximum daily amount - 3 or more alcoholic drinks every day while using this product

Stomach bleeding warning: This product contains an NSAID, which may cause severe stomach bleeding.The chance is higher if you:

- are age 60 or older
- take more or for a longer time than directed

- have had stomach ulcers or bleeding problems
- take a blood thinning (anticoagulant) or steroid drug

- take other drugs containing prescription or nonprescription NSAIDs [aspirin, ibuprofen, naproxen, or others]

- have 3 or more alcoholic drinks every day while using this product

Caffeine warning: The recommended dose of this product contains about as much caffeine as a cup of coffee. Limit the use of caffeine-containing medications, foods, or beverages while taking this product because too much caffeine may cause nervousness, irritability, sleeplessness, and, occasionally, rapid heartbeat.

Do not use

- if you have ever had an allergic reaction to acetaminophen, aspirin, or any other pain reliever/fever reducer

- with any other drug containing acetaminophen (prescription or nonprescription). If you are not sure whether a drug contains acetaminophen, ask a doctor or pharmacist.

Ask a doctor before use if

-you have liver disease
-stomach bleeding warning applies to you

- you have a history of stomach problems, such as heartburn

- you have high blood pressure, heart disease, liver cirrhosis, or kidney disease
- you have asthma

- you are taking a diuretic

Ask a doctor or pharmacist before use if you are

- taking a prescription drug for diabetes, gout, or arthritis

- taking any other drug or are under a doctor's care for any serious condition

Stop use and ask a doctor if

- an allergic reaction occurs. Seek medical help right away.

- you experience any of the following signs of stomach bleeding: - feel faint - have bloody or black stools - vomit blood - have stomach pain that does not get better - ringing in the ears or loss of hearing occurs
- pain gets worse or lasts for more than 10 days
- fever gets worse or lasts for more than 3 days
- painful area is red or swollen

- any new symptoms appear.

These could be signs of a serious condition.

If pregnant or breast-feeding,

ask a health professional before use. It is especially important not to use aspirin during the last 3 months of pregnancy unless definitely directed to do so by a doctor because it may cause problems in the unborn child or complications during delivery.

Keep out of reach of children

In case of accidental overdose,

get medical help or contact a Poison Control Center (1-800-222-1222) right away. Prompt medical attention is critical for adults as well as for children even if you do not notice any signs or symptoms.

Directions

- Do not use more than directed
- Drink a full glass of water with each dose
- Adults and children 12 years and over:
. take 2 caplets every 6 hours
. do not take more than 8 caplets in 24 hours
- Children under 12 years: ask a doctor

Other information

- store in a dry place at 15° -30°C (59° - 86°F)
- use by expiration date on package

Inactive ingredients

hypromellose, maltodextrin, microcrystalline cellulose, polydextrose, polyvinylpyrrolidone, pregelatinized starch, silica, starch, stearic acid, talc, titanium dioxide, triglycerides

Questions or comments?

855-280-1079

t This product is not manufactured or distributed by Haleon, owner of the registered trademark Excedrin®.
Distributed by:
FARMACIAS DE SIMILARES TX LLC
800 Brazos St Ste 260, Austin, TX, 78701, USA
customerservice@drsimi.com
www.drsimi.com

PACKAGE LABEL

Dr. Simi

NDC: 85786-105-90

Compare to Excedrin® Extra Strength Headache Relief Active ingredients t

Extra Strength Acetaminophen 250 mg, Aspirin 250 mg (NSAID)* and Caffeine 65 mg

Pain Reliever / Pain Reliever Aid

100 Caplets